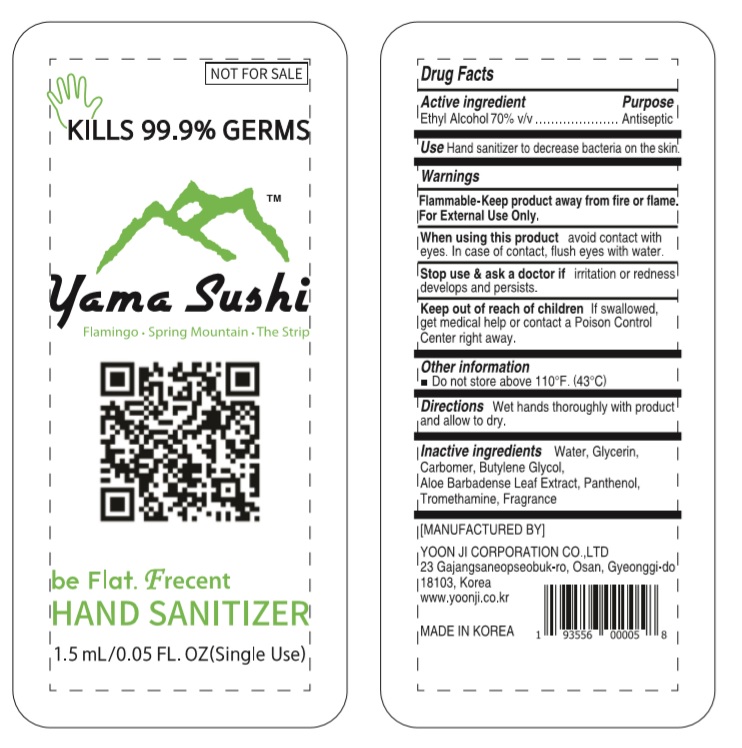 DRUG LABEL: be Flat. Frecent HAND SANITIZER
NDC: 75024-715 | Form: GEL
Manufacturer: YOON JI CORPORATION CO.,LTD
Category: otc | Type: HUMAN OTC DRUG LABEL
Date: 20200702

ACTIVE INGREDIENTS: ALCOHOL 1.05 mL/1.5 mL
INACTIVE INGREDIENTS: BUTYLENE GLYCOL; ALOE VERA LEAF; GLYCERIN; CARBOMER HOMOPOLYMER, UNSPECIFIED TYPE; WATER; PANTHENOL; TROLAMINE

be Flat. Frecent HAND SANITIZER 1.5 ml x 1: 75024-715-01